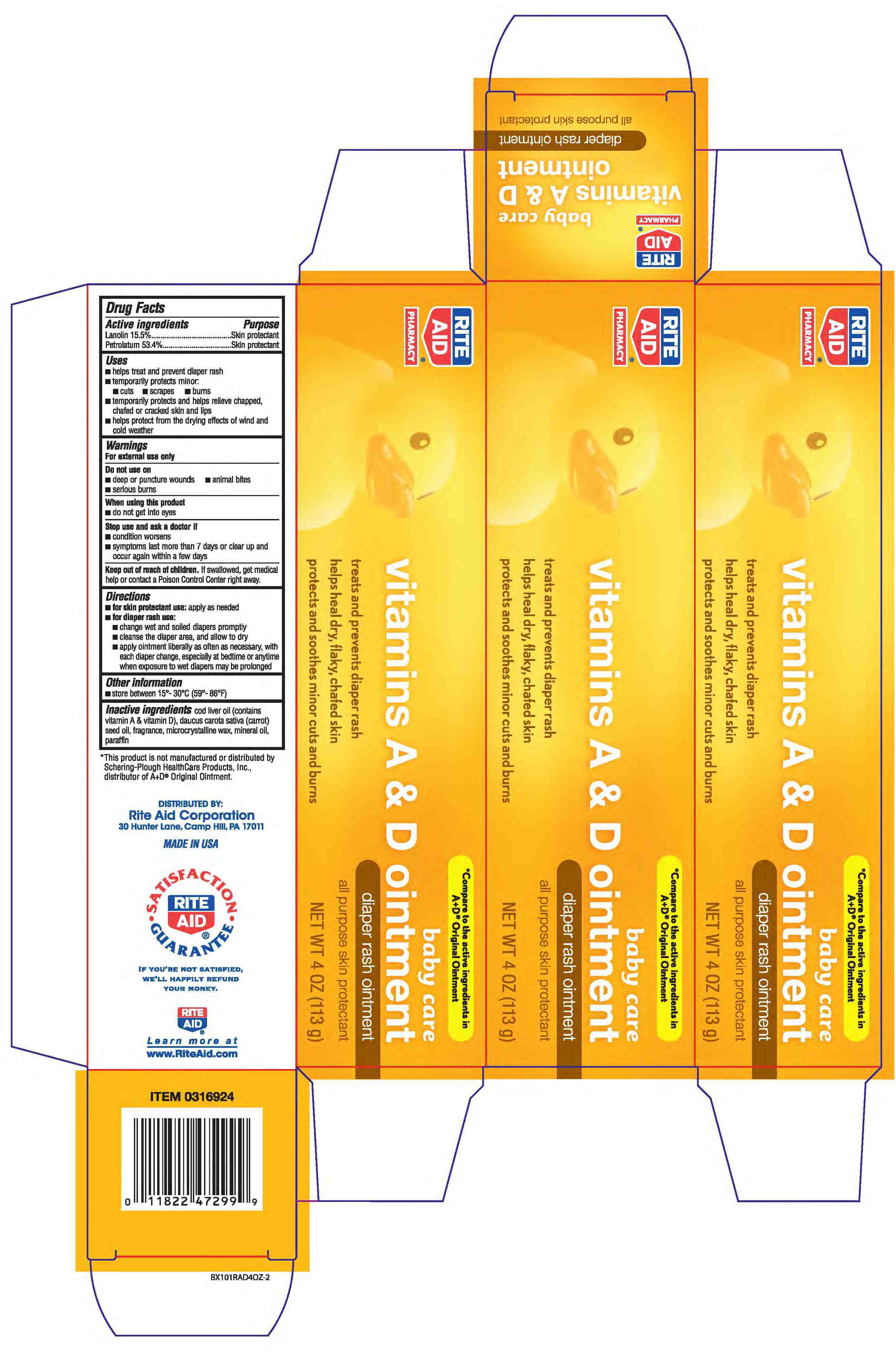 DRUG LABEL: PETROLATUM and LANOLIN
NDC: 11822-0684 | Form: OINTMENT
Manufacturer: RiteAid
Category: otc | Type: HUMAN OTC DRUG LABEL
Date: 20110216

ACTIVE INGREDIENTS: PETROLATUM .534 g/1 g; LANOLIN .155 g/1 g
INACTIVE INGREDIENTS: PARAFFIN ; MICROCRYSTALLINE WAX; MINERAL OIL; COD LIVER OIL; CARROT SEED OIL

drug facts

Active ingredient Purpose
Lanolin 15.5% ..................................................Skin protectant
Petrolatum 53.4%.............................................Skin protectant

Active ingredient Purpose
Lanolin 15.5% ..................................................Skin protectant
Petrolatum 53.4%.............................................Skin protectant
Uses
- Helps treat and prevent diaper rash
- temporarily protects minor - cuts - scrapes - burns
- temporarily protects and helps relieve chapped, chafed or cracked skin and lips
- helps protect from the drying effects of wind and cold weather

Keep out of the reach of children.
If swallowed, get medical help or contact
a Poison Control Center right away.

Uses
- Helps treat and prevent diaper rash
- temporarily protects minor - cuts - scrapes - burns
- temporarily protects and helps relieve chapped, chafed or cracked skin and lips
- helps protect from the drying effects of wind and cold weather

Warnings
For external use only.
Do not use on:
- deep or puncture wounds
- animal bites - serious burns
When using this product - Do not get into eyes
Stop use and ask a doctor if:
-condition worsens
-symptoms last more than 7 days or clear
up and occur again within a few days
Keep out of reach of children. If swallowed, get medical help or
contact a Poison Control Center right away.

Directions
- for skin protectant use: apply as needed
- For diaper rash use:
- change wet and soiled diapers promptly
- cleanse the diaper area and allow to dry
- apply ointment liberally as often as necessarry with
each diaper change, especially at bedtime or anytime
when exposure to wet diapers may be prolonged
Other information
Store between 15 degrees - 30 degrees C (59 degrees - 86 degrees F)

INACTIVE INGREDIENT

Inactive ingredients cod liver oil (contains vitamin A and vitamin D)
daucus carota (carot) seed oil, fragrance, microcrystalline wax, mineral oil, paraffin